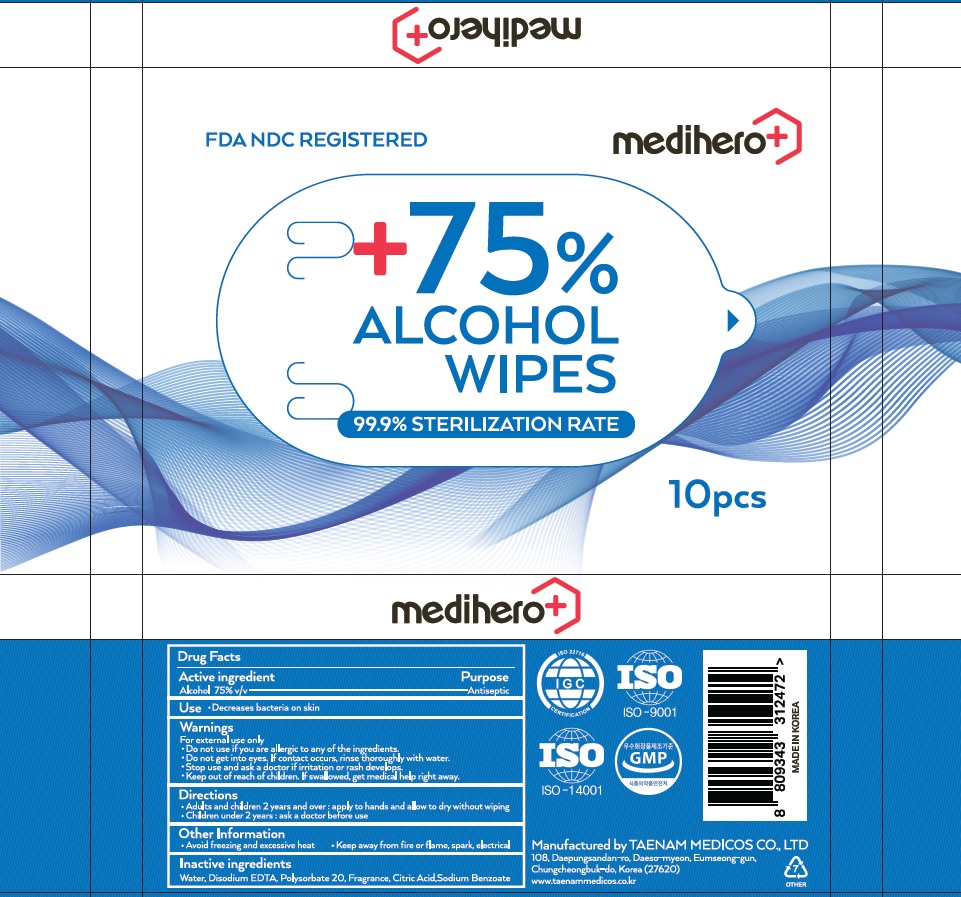 DRUG LABEL: MEDIHERO 75 PERCENT ALCOHOL WIPES
NDC: 70894-100 | Form: CLOTH
Manufacturer: TAENAM MEDICOS CO., LTD.
Category: otc | Type: HUMAN OTC DRUG LABEL
Date: 20200624

ACTIVE INGREDIENTS: Alcohol 0.75 1/1 1
INACTIVE INGREDIENTS: Water; EDETATE DISODIUM ANHYDROUS; Polysorbate 20; CITRIC ACID MONOHYDRATE; Sodium Benzoate

ACTIVE INGREDIENT

Alcohol 75% v/v

INACTIVE INGREDIENTS

Water, Disodium EDTA, Polysorbate 20, Fragrance, Citric Acid, Sodium Benzoate

PURPOSE

Antiseptic

WARNINGS

For external use only
Do not use if you are allergic to any of the ingredients.
Do not get into eyes. If contact occurs, rinse thoroughly with water.
Stop use and ask a doctor if irritation or rash develops.
Keep out of reach of children. If swallowed, get medical help right away.

KEEP OUT OF REACH OF CHILDREN

If swallowed, get medical help right away.

Uses

Decreases bacteria on skin

Directions

Adults and children 2 years and over : apply to hands and allow to dry without wiping
Children under 2 years : ask a doctor before use

Other Information

Avoid freezing and excessive heat
Keep away from fire or flame, spark, electrical